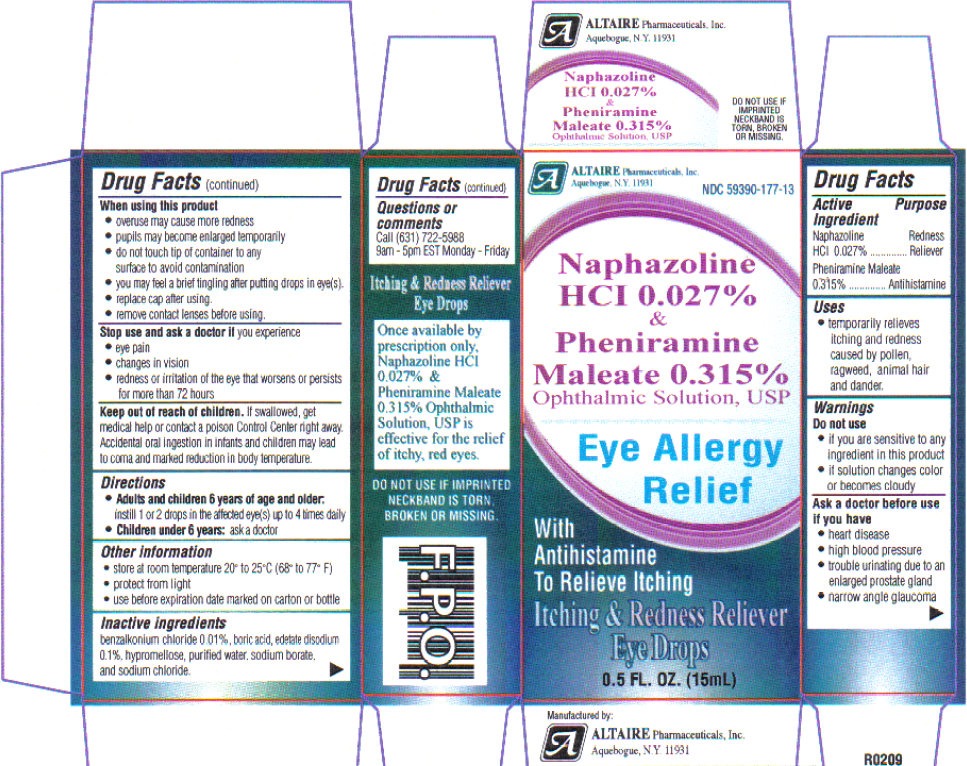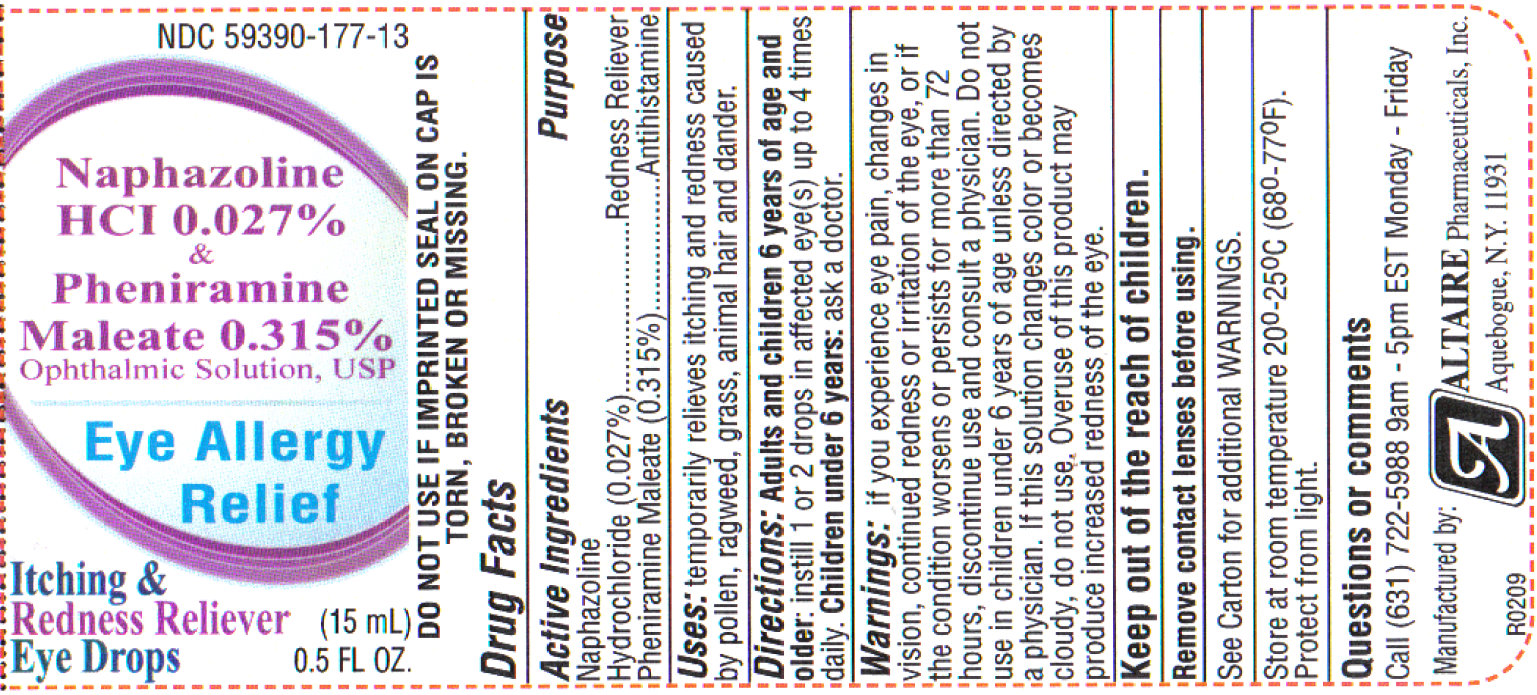 DRUG LABEL: Naphazoline HCI And Pheniramine Maleate
NDC: 59390-177 | Form: SOLUTION/ DROPS
Manufacturer: Altaire Pharmaceuticals Inc.
Category: otc | Type: HUMAN OTC DRUG LABEL
Date: 20201228

ACTIVE INGREDIENTS: NAPHAZOLINE HYDROCHLORIDE 0.27 mg/1 mL; PHENIRAMINE MALEATE 3.15 mg/1 mL
INACTIVE INGREDIENTS: BENZALKONIUM CHLORIDE; BORIC ACID; EDETATE DISODIUM; HYPROMELLOSE, UNSPECIFIED; WATER; SODIUM BORATE; SODIUM CHLORIDE

Naphazoline HCI 0.027% & Pheniramine Maleate 0.315% Ophthalmic Solution, USP

Active Ingredients

Naphazoline Hydrochloride (0.027%)

Pheniramine Maleate (0.315%)

Purpose

Redness Reliever

Antihistamine

INDICATIONS AND USAGE

Uses: temporarily relieves itching and redness caused by pollen, ragweed, grass, animal hair and dander.

WARNINGS

Warnings: if you experience eye pain, changes in vision, continued redness or irritation of the eye, or if the condition worsens or persists for more than 72 hours, discontinue use and consult a physician. Do not use in children under 6 years of age unless directed by a physician. If this solution changes color or becomes cloudy, do not use. Overuse of this product may produce increased redness of the eye.

If you are sensitive to any ingredient in this product, do not use. To avoid contamination, do not touch tip of container to any surface. Replace cap after using.

Do not use if imprinted seal on cap is torn, broken or missing, or if imprinted seals on top ad bottom flaps are not intact and completely legible.

Ask a doctor before use if you have

- heart disease
- high blood pressure
- trouble urinating due to enlarged prostrate gland
- narrow angle glaucoma

Remove contact lenses before using.

Stop use and ask a doctor if you experience: eye pain, changes in vision, redness or irritation of the eye that worsens or persists for more than 72 hours. Overuse of this product may produce increased redness of the eye. Pupils may become enlarged temporarily. You may experience a brief tingling sensation after putting drops in eyes.

Keep out of reach of children.

In case of accidental ingestion, seek professional assistance or contact a Poison Control Center immediately. Accidental oral ingestion in infants and children may lead to coma and marked reduction in body temperature.

Directions:

Adults and children 6 years of age and older: instill 1 or 2 drops in affected eye(s) up to 4 times daily.

Children under 6 years: ask a doctor.

STORAGE AND HANDLING

Store at room temperature 20 degrees - 25 degrees C (68 degrees - 77 degrees F).

Protect from light.

Use before expiration date marked on the carton or bottle.

Available in 15mL NDC 59390-177-13 and 30 mL NDC 59390-177-18

Inactive ingredients

benzalkonium chloride 0.01%, boric acid, edetate disodium 0.1%, hypromellose, purified water, sodium borate, and sodium chloride.

Questions or comments

Call (631) 722-5988 9am - 5pm EST Monday - Friday

Manufactured by:

Altaire Pharmaceuticals, Inc.

Aquebogue, N.Y. 11931

PACKAGE LABEL

ALTAIRE Pharmaceuticals, Inc.

Aquebogue, N.Y. 11931

Naphazoline HCI 0.027%

and

Pheniramine Maleate 0.315%

Ophthalmic Solution, USP

Eye Allergy Relief

With Antihistamine To Relieve Itching

Itching and Redness Reliever
Eye Drops

0.5 Fl. OZ. (15mL)